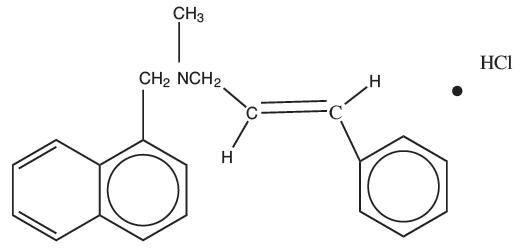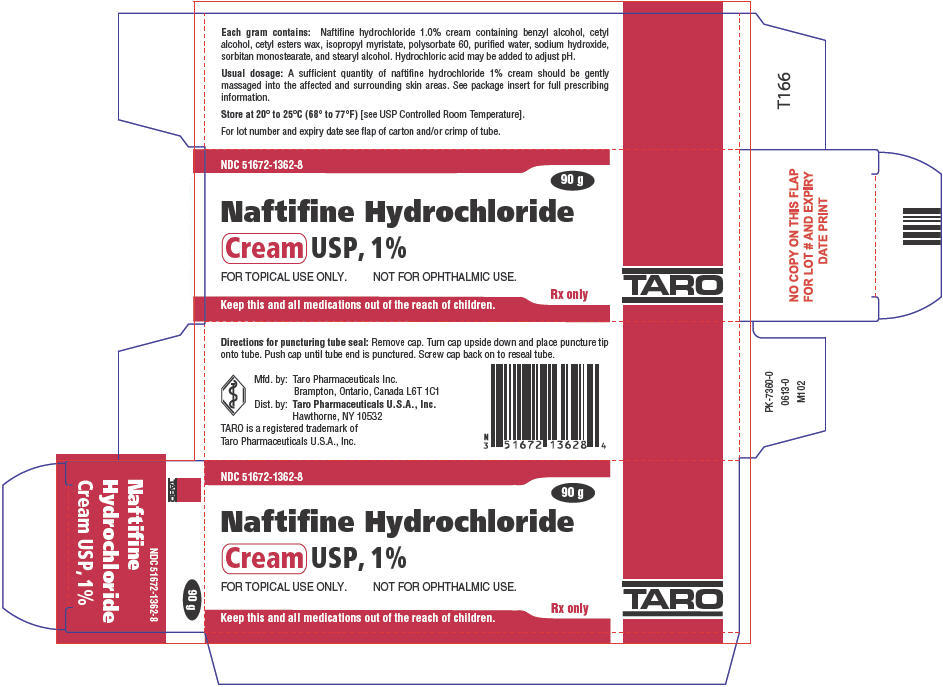 DRUG LABEL: Naftifine Hydrochloride
NDC: 51672-1362 | Form: CREAM
Manufacturer: Sun Pharmaceutical Industries, Inc.
Category: prescription | Type: HUMAN PRESCRIPTION DRUG LABEL
Date: 20250707

ACTIVE INGREDIENTS: NAFTIFINE HYDROCHLORIDE 10 mg/1 g
INACTIVE INGREDIENTS: BENZYL ALCOHOL; CETYL ALCOHOL; CETYL ESTERS WAX; ISOPROPYL MYRISTATE; POLYSORBATE 60; SODIUM HYDROXIDE; WATER; SORBITAN MONOSTEARATE; STEARYL ALCOHOL; HYDROCHLORIC ACID

Naftifine Hydrochloride
Cream USP, 1%

Rx ONLY

DESCRIPTION

Naftifine Hydrochloride Cream USP, 1% contains the synthetic, broad-spectrum, antifungal agent naftifine hydrochloride. Naftifine Hydrochloride Cream USP, 1% is for topical use only.

CHEMICAL NAME:

(E)-N-Cinnamyl-N-methyl-1-naphthalenemethylamine hydrochloride. Naftifine hydrochloride has an empirical formula of C21H21N∙HCl and a molecular weight of 323.86.

Structural Formula

naftifine hydrochloride

Contains

Active Ingredient

Naftifine hydrochloride 1%

Inactive Ingredients

benzyl alcohol, cetyl alcohol, cetyl esters wax, isopropyl myristate, polysorbate 60, purified water, sodium hydroxide, sorbitan monostearate, and stearyl alcohol. Hydrochloric acid may be added to adjust pH.

CLINICAL PHARMACOLOGY

Naftifine hydrochloride is a synthetic allylamine derivative. The following in vitrodata are available, but their clinical significance is unknown. Naftifine hydrochloride has been shown to exhibit fungicidal activity in vitroagainst a broad spectrum of organisms, including Trichophyton rubrum, Trichophyton mentagrophytes, Trichophyton tonsurans, Epidermophyton floccosum, Microsporum canis, Microsporum audouini,and Microsporum gypseum;and fungistatic activity against Candidaspecies, including Candida albicans. Naftifine Hydrochloride Cream USP, 1% has only been shown to be clinically effective against the disease entities listed in the INDICATIONS AND USAGE section.

Although the exact mechanism of action against fungi is not known, naftifine hydrochloride appears to interfere with sterol biosynthesis by inhibiting the enzyme squalene 2, 3-epoxidase. This inhibition of enzyme activity results in decreased amounts of sterols, especially ergosterol, and a corresponding accumulation of squalene in the cells.

Pharmacokinetics

In vitroand in vivobioavailability studies have demonstrated that naftifine penetrates the stratum corneum in sufficient concentration to inhibit the growth of dermatophytes.

Following a single topical application of 1% naftifine cream to the skin of healthy subjects, systemic absorption of naftifine was approximately 6% of the applied dose. Naftifine and/or its metabolites are excreted via the urine and feces with a half-life of approximately two to three days.

INDICATIONS AND USAGE

Naftifine Hydrochloride Cream USP, 1% is indicated for the topical treatment of tinea pedis, tinea cruris and tinea corporis caused by the organisms Trichophyton rubrum, Trichophyton mentagrophytes,and Epidermophyton floccosum.

CONTRAINDICATIONS

Naftifine Hydrochloride Cream USP, 1% is contraindicated in individuals who have shown hypersensitivity to any of its components.

WARNINGS

Naftifine Hydrochloride Cream USP, 1% is for topical use only and not for ophthalmic use.

PRECAUTIONS

General

Naftifine Hydrochloride Cream USP, 1% is for external use only. If irritation or sensitivity develops with the use of Naftifine Hydrochloride Cream USP, 1%, treatment should be discontinued and appropriate therapy instituted.

Diagnosis of the disease should be confirmed either by direct microscopic examination of a mounting of infected tissue in a solution of potassium hydroxide or by culture on an appropriate medium.

Information for patients

The patient should be told to:

1. Avoid the use of occlusive dressings or wrappings unless otherwise directed by the physician.
2. Keep Naftifine Hydrochloride Cream USP, 1% away from the eyes, nose, mouth and other mucous membranes.

Carcinogenesis, mutagenesis, impairment of fertility

In a 2-year dermal carcinogenicity study, naftifine hydrochloride cream was administered to Sprague-Dawley rats at topical doses of 1%, 2% and 3% (10 mg/kg/day, 20 mg/kg/day, and 30 mg/kg/day naftifine hydrochloride). No drug-related tumors were noted in this study up to the highest dose evaluated in this study of 30 mg/kg/day [3.6 times the maximum recommended human dose (MRHD) based on mg/m^2comparison].

Naftifine hydrochloride revealed no evidence of mutagenic or clastogenic potential based on the results of two in vitrogenotoxicity tests (Ames assay and Chinese hamster ovary cell chromosome aberration assay) and one in vivogenotoxicity test (mouse bone marrow micronucleus assay).

Oral administration of naftifine hydrochloride to rats, throughout mating, gestation, parturition and lactation, demonstrated no effects on growth, fertility or reproduction, at doses up to 100 mg/kg/day (12 times MRHD based on mg/m^2comparison).

Pregnancy

Teratogenic Effects

Reproduction studies have been performed in rats and rabbits (via oral administration) at doses 150 times or more than the topical human dose and have revealed no evidence of impaired fertility or harm to the fetus due to naftifine. There are, however, no adequate and well-controlled studies in pregnant women. Because animal reproduction studies are not always predictive of human response, this drug should be used during pregnancy only if clearly needed.

Nursing mothers

It is not known whether this drug is excreted in human milk. Because many drugs are excreted in human milk, caution should be exercised when Naftifine Hydrochloride Cream USP, 1% is administered to a nursing woman.

Pediatric use

Safety and effectiveness in pediatric patients have not been established.

ADVERSE REACTIONS

During clinical trials with Naftifine Hydrochloride Cream USP, 1%, the incidence of adverse reactions was as follows: burning/stinging (6%), dryness (3%), erythema (2%), itching (2%), local irritation (2%).

DOSAGE AND ADMINISTRATION

A sufficient quantity of Naftifine Hydrochloride Cream USP, 1% should be gently massaged into the affected and surrounding skin areas once a day. The hands should be washed after application. If no clinical improvement is seen after four weeks of treatment with Naftifine Hydrochloride Cream USP, 1%, the patient should be re-evaluated.

HOW SUPPLIED

Naftifine Hydrochloride Cream USP, 1% is supplied in the following sizes:
15 g - NDC 51672-1362-1 (tube)
30 g - NDC 51672-1362-2 (tube)
60 g - NDC 51672-1362-3 (tube)
90 g - NDC 51672-1362-8 (tube)

STORAGE AND HANDLING

Store at 20° to 25°C (68° to 77°F)[see USP Controlled Room Temperature].

Manufactured by:
Taro Pharmaceuticals Inc., Brampton, Ontario, Canada L6T 1C1

Distributed by:
Taro Pharmaceuticals U.S.A., Inc.,Hawthorne, NY 10532

TARO is a registered trademark of Taro Pharmaceuticals U.S.A., Inc.

Revised: May 2018
PK-7357-2 10

PRINCIPAL DISPLAY PANEL - 90 g Tube Carton

NDC 51672-1362-8

90 g

Naftifine Hydrochloride
Cream USP, 1%

FOR TOPICAL USE ONLY.
NOT FOR OPHTHALMIC USE.

Rx only

TARO

Keep this and all medications out of the reach of children.